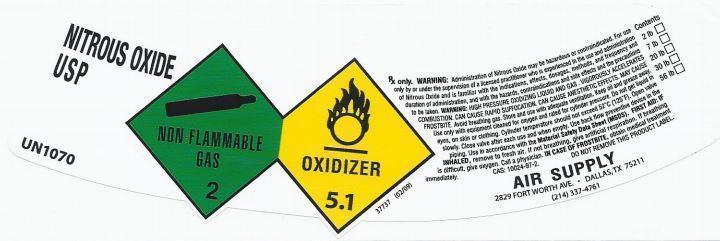 DRUG LABEL: Nitrous Oxide
NDC: 63978-201 | Form: GAS
Manufacturer: Quality Air Products Inc
Category: prescription | Type: HUMAN PRESCRIPTION DRUG LABEL
Date: 20251209

ACTIVE INGREDIENTS: NITROUS OXIDE 990 mL/1 L

Nitrous Oxide

PACKAGE LABEL

Nitrous Oxide
USP

UN1070

Non-flammable gas, 2
Oxidizer, 5.1

Rx only. Warning: Administration of nitrous oxide may be hazardous or contraindicated. For use only by or under the supervision of a licensed practitioner who is experienced in the use and administration of Nitrous Oxide and is familiar with the indications, effects, dosages, methods, and frequency and duration of administration, and with the hazards, contraindications and side effects and the precautions to be taken. Warning: HIGH PRESSURE OXIDING LIQUID AND GAS. VIGOROUSLY ACCELERATES COMBUSTION. CAN CAUSE RAPID SUFFOCATION. CAN CAUSE ANESTHETIC EFFECTS. MAY CAUSE FROSTBITE. Avoid breathing gas. Store and use with adequate ventilation. Keep oil and grease away. Use only with equipment cleaned for oxygen and rated for cylinder pressure. Do not get liquid in eyes, on skin or clothing. Cylinder temperature should not exceed 52˚C (125˚F). Open valve slowly. Close valve after each use and when empty. Use back flow preventive device in the piping. Use in accordance with the Material Safety Data Sheet (MSDS). First Aid: IF INHALED, remove to fresh air. If not breathing, give artificial respiration. If breathing is difficult, give oxygen. Call a physician. IN CASE OF FROSTBITE, obtain medical treatment immediately. CAS: 10024-97-2. DO NOT REMOVE THIS PRODUCT LABEL.

AIR SUPPLY
2829 Fort Worth Ave Dallas, TX 75211
(214) 337-4761

Contents
2 lb
7 lb
20 lb
30 lb
56 lb